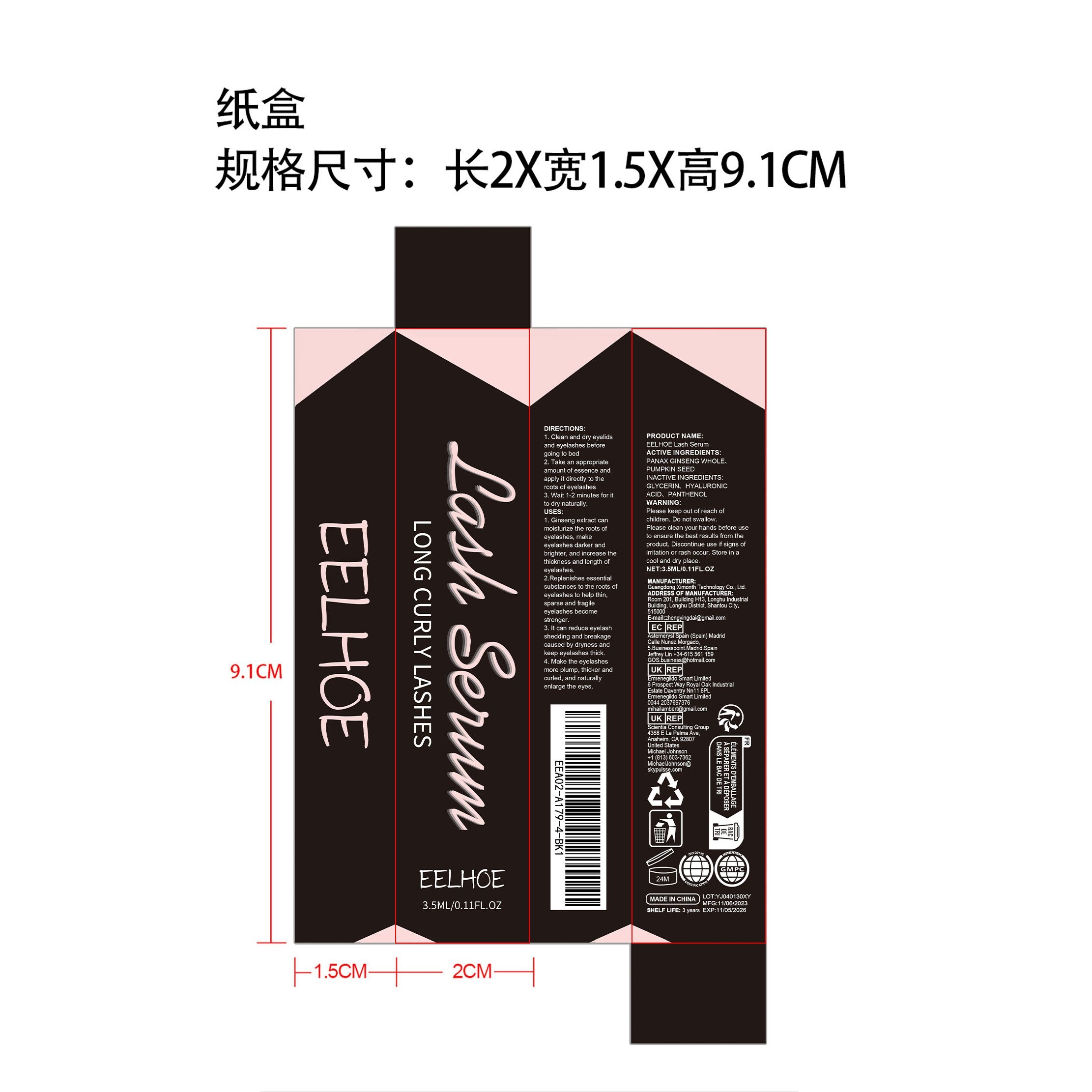 DRUG LABEL: EELHOE Lash Serum
NDC: 84660-051 | Form: LIQUID
Manufacturer: Guangdong Ximonth Technology Co., Ltd.
Category: otc | Type: HUMAN OTC DRUG LABEL
Date: 20241028

ACTIVE INGREDIENTS: PUMPKIN SEED 0.525 mg/3.5 mg; PANAX GINSENG WHOLE 0.7 mg/3.5 mg
INACTIVE INGREDIENTS: HYALURONIC ACID 0.875 mg/3.5 mg; PANTHENOL 0.35 mg/3.5 mg; GLYCERIN 1.05 mg/3.5 mg

Active Ingredient(s)

PANAX GINSENG WHOLE、PUMPKIN SEED

Purpose

1. Ginseng extract can moisturize the roots of eyelashes, make eyelashes darker and brighter, and increase the thickness and length of eyelashes.
2.Replenishes essential substances to the roots of eyelashes to help thin, sparse and fragile eyelashes become stronger.
3. It can reduce eyelash shedding and breakage caused by dryness and keep eyelashes thick.
4. Make the eyelashes more plump, thicker and curled, and naturally enlarge the eyes.

Use

1. Clean and dryeyelids and eyelashesbefore going to bed
2. Take an appropriateamount of essenceand apply it directly to
3. Wait 1-2 minutes for it to dry naturally.the roots of eyelashes

Warnings

Please keep out of reach of children.Do not swallow.Please clean your hands before use to ensure the best results from the product.Discontinue use if signs of irritation or rash occur.Store in a cool and dry place.

Do not use

Discontinue use if signs of irritation or rash occur.

Stop Use

Discontinue use if signs of irritation or rash occur.

KEEP OUT OF REACH OF CHILDREN

Please keep out of reach of children. Do not swallow.

STORAGE AND HANDLING

Store in a cool and dry place.

INACTIVE INGREDIENT

GLYCERIN、HYALURONIC ACID、PANTHENOL